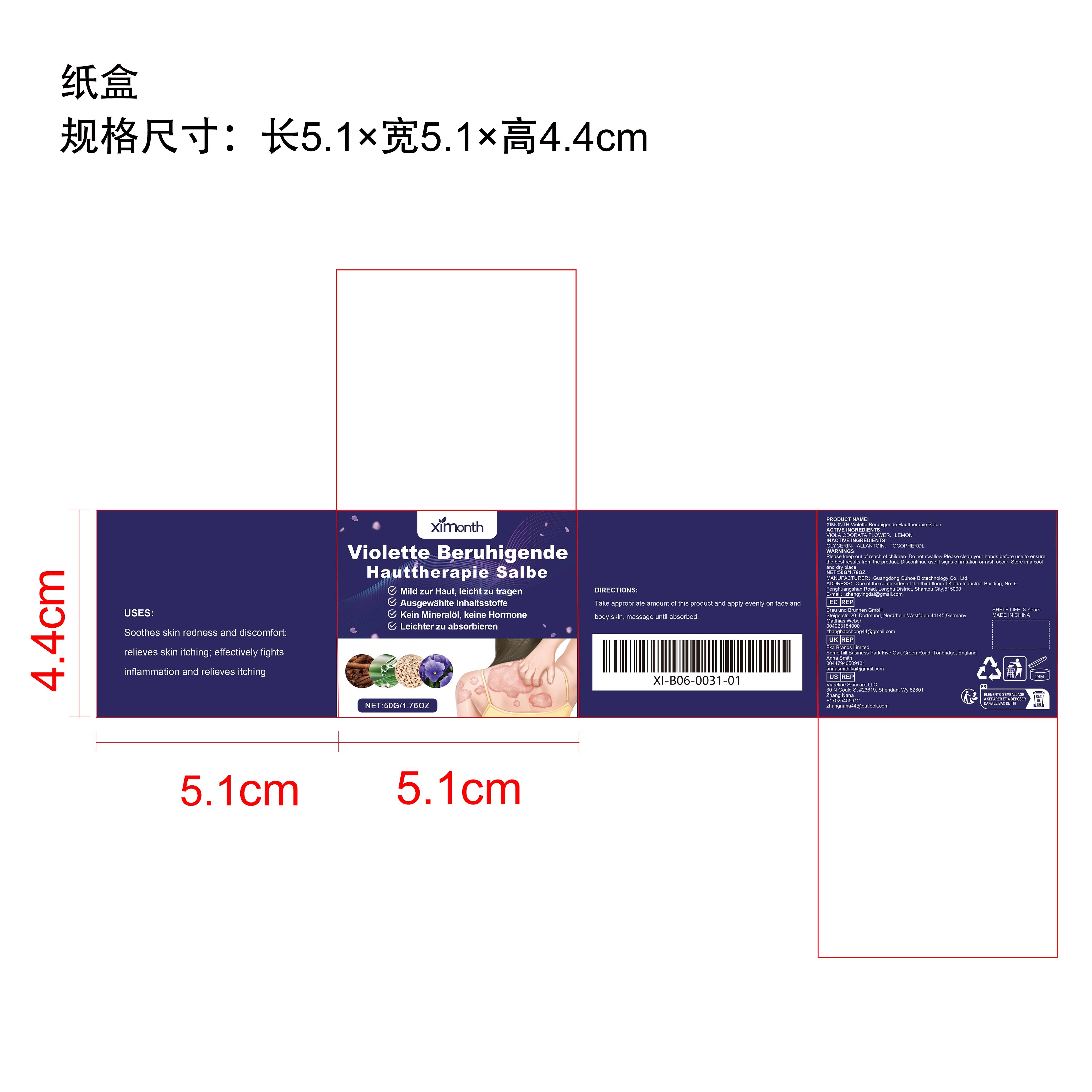 DRUG LABEL: XIMONTH Violette Beruhigende Hauttherapie Salbe
NDC: 84744-057 | Form: CREAM
Manufacturer: Guangdong Ouhoe Biotechnology Co., Ltd.
Category: otc | Type: HUMAN OTC DRUG LABEL
Date: 20241022

ACTIVE INGREDIENTS: LEMON 5 g/50 g; VIOLA ODORATA FLOWER 10 g/50 g; TOCOPHEROL 5 g/50 g
INACTIVE INGREDIENTS: GLYCERIN 20 g/50 g; ALLANTOIN 10 g/50 g

Active Ingredient(s)

VIOLA ODORATA FLOWER、LEMON、TOCOPHEROL

Purpose

Soothes skin redness and discomfort;relieves skin itching; effectively fightsinflammation and relieves itching

Use

Take appropriate amount of this product and apply evenly on face and body skin, massage until absorbed.

Warnings

Please keep out of reach of children.Do not swallow.Please clean your hands before use to ensure the best results from the product.Discontinue use if signs of irritation or rash occur.Store in a cool and dry place.

Do not use

Discontinue use if signs of irritation or rash occur.

Stop Use

Discontinue use if signs of irritation or rash occur.

KEEP OUT OF REACH OF CHILDREN

Please keep out of reach of children. Do not swallow.

STORAGE AND HANDLING

Store in a cool and dry place.

INACTIVE INGREDIENT

GLYCERIN、ALLANTOIN